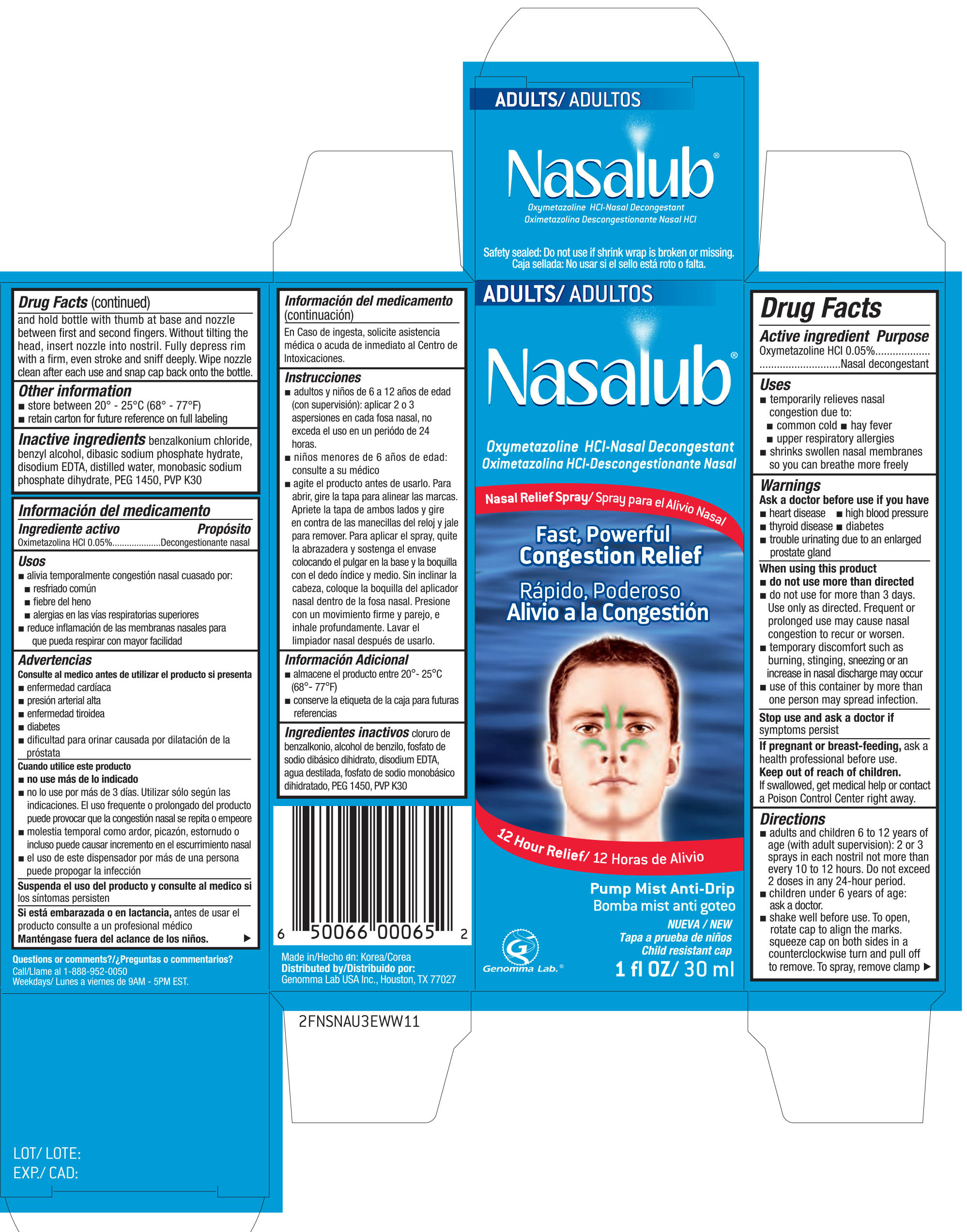 DRUG LABEL: Nasalub Nasal Relief
NDC: 50066-065 | Form: SPRAY
Manufacturer: Genomma Lab USA, Inc
Category: otc | Type: HUMAN OTC DRUG LABEL
Date: 20161107

ACTIVE INGREDIENTS: OXYMETAZOLINE HYDROCHLORIDE .05 g/100 mL
INACTIVE INGREDIENTS: BENZALKONIUM CHLORIDE; BENZYL ALCOHOL; SODIUM PHOSPHATE, DIBASIC, DIHYDRATE; EDETATE DISODIUM; WATER; SODIUM PHOSPHATE, MONOBASIC, DIHYDRATE; POLYETHYLENE GLYCOL 1450; POVIDONE K30

Active ingredient Purpose

Oxymetazoline HCL 0.05%................................... Nasal decongestant

Uses

- temporarily relieves nasal congestion due to:
- common cold
- hay fever
- upper respiratory allergies
- shrinks swollen nasal membranes so you can breathe more freely

Warnings

Ask a doctor before use if you have

- heart disease
- high blood pressure
- thyroid disease
- diabetes
- trouble urinating due to an enlarged prostate gland

When using this product

- do not use more directed. Use only as directed. Frequent or prolonged use may cause nasal congestion to recur or worsen.
- temporary discomfort such as burning, stinging, sneezing or an icrease in nasal discharge may occur
- use of this container by more than one person may spread infection

Stop use and ask a doctor if symptoms persist

PREGNANCY OR BREAST FEEDING

If pregnant or breast-feeding, ask a health professional before use

Keep out of reach of children. If swallowed, get medical help or contact a Poison Control Center right away.

Directions

- adults and children 6 to 12 years of age (with adult supervision): 2 or 3 sprays in each nostril not more than every 10 to 12 hours. Do not exceed 2 doses in any 24-hour period
- children under 6 years of age: ask a doctor
- shake well before use. To open, rotate cap to align the marks. squeeze cap on both sides in a counterclockwise turn and pull off to remove. To spray, remove clamp and hold bottle with thumb at base and nozzle between first and second fingers. Without tiliting the head, insert nozzle into nostril. Fully depress rim with a firm, een stroke and sniff deeply. Wipe nozzle clean after each use and sanp cab back onto the bottle.

Other information

- store between 20° and 25°C (68° and 77°F)
- retain carton for future reference on full labeling

Inactive ingredients

benzalkonium chloride, benzyl alcohol, dibasic sodium phospahte hydrate, disodium EDTA, distilled water, monobasic sodium phosphate dihydrate, PEG 1450, PVP K30

DOSAGE AND ADMINISTRATION

DISTRIBUTED BY:

GENOMMA LAB USA INC.

HOUSTON, TX 77027

MADE IN KOREA